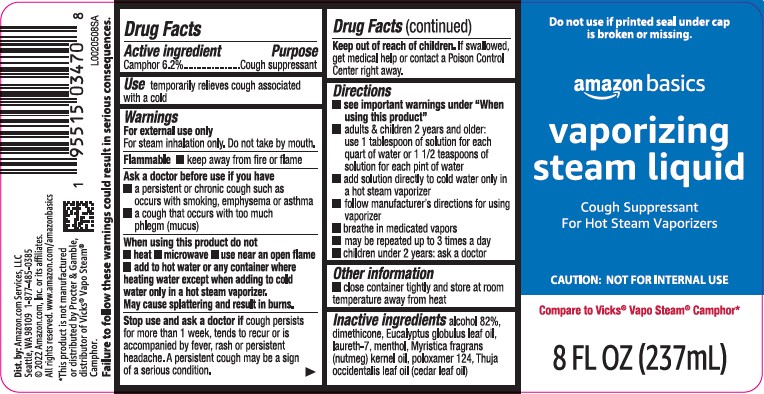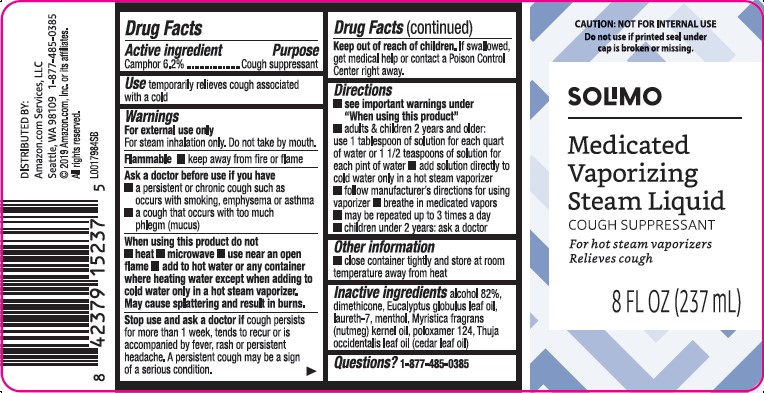 DRUG LABEL: Vaporizing
NDC: 72288-397 | Form: INHALANT
Manufacturer: Amazon.com Services LLC
Category: otc | Type: HUMAN OTC DRUG LABEL
Date: 20250414

ACTIVE INGREDIENTS: CAMPHOR (SYNTHETIC) 62 mg/1 mL
INACTIVE INGREDIENTS: ALCOHOL; DIMETHICONE; EUCALYPTUS OIL; LAURETH-7; MENTHOL; NUTMEG OIL; POLOXAMER 124; CEDAR LEAF OIL

Basics_Solimo 397.002/397AA rev 2-397AB
Medicated Vaporizing Steam Liquid

safety information

FAILURE TO FOLLOW THESE WARNINGS COULD RESULT IN SERIOUS CONSEQUENCES

Active Ingredient

Camphor 6.2%

Purpose

Cough suppressant

Use

temporarily relieves cough associated with a cold

Warnings

For external use only

For steam inhalation only. Do not take by mouth.

Flammable

- keep away from fire or flame.

Ask a doctor before use if you have

- a persistent or chronic cough such as occurs with smoking, emphysema or asthma
- a cough that occurs with too much phlegm (mucus)

When using this product do not

- heat
- microwave
- use near an open flame
- add to hot water or any container where heating water except when adding to cold water only in a hot steam vaporizer. May cause splattering and result in burns.

Stop use and ask a doctor

if cough persists for more than 1 week, tends to recur or is accompanied by fever, rash, or persistent headache. A persistent cough may be a sign of a serious condition.

Keep out of reach of children.

If swallowed, get medical or contact a Poison Control Center right away.

Directions

- see important warnings under "When using this product"
- adults & children 2 years and older: use 1 tablespoon of solution for each quart of water or 1 1/2 teaspoons of solution for each pint of water
- add solution directly to cold water only in a hot steam vaporizer
- follow manufacturer's directions for using vaporizer
- breath in medicated vapors
- may be repeated up to 3 times a day
- children under 2 years: ask a doctor

Other information

- close container tightly and store at room temperature away from heat

Inactive ingredients

alcohol 82%, dimethicone, Eucalyptus globulus leaf oil, laureth-7, menthol, Myristica fragrans (nutmeg) kernel oil,
poloxamer 124, Thuja occidentalis leaf oil (cedar leaf oil)

ADVERSE REACTION

Dist. BY: Amazon.com Services, LLC

Seattle, WA 98109 1-877-485-0385

©2022 Amazon.com, Inc. or its affiliates.

All rights reserved. www.amazon.com/amazonbasics

Disclaimer

*This product is not manufactured or distributed by Proctor & Gamble, distibuter of Vicks®Vapo Steam®Camphor.

Pincipal Display Panel

CAUTION: NOT FOR INTERNAL USE

Do not use if printed seal under cap is broken or missing

SOLIMO

Medicated

Vaporizing

Steam Liquid

COUGH SUPPRESSANT

For hot steam vaporizers

Relieves cough

8 FL OZ (237 mL)

Pincipal Display Panel

Do not use if printed seal under cap is broken or missing.

amazon basics

vaporizing

steam liquid

Cough Suppressant

For Hot Steam Vaporizers

CAUTION: NOT FOR INTERNAL USE

Compare to Vicks®Vapo Steam®Camphor

8 FL OZ (237mL)